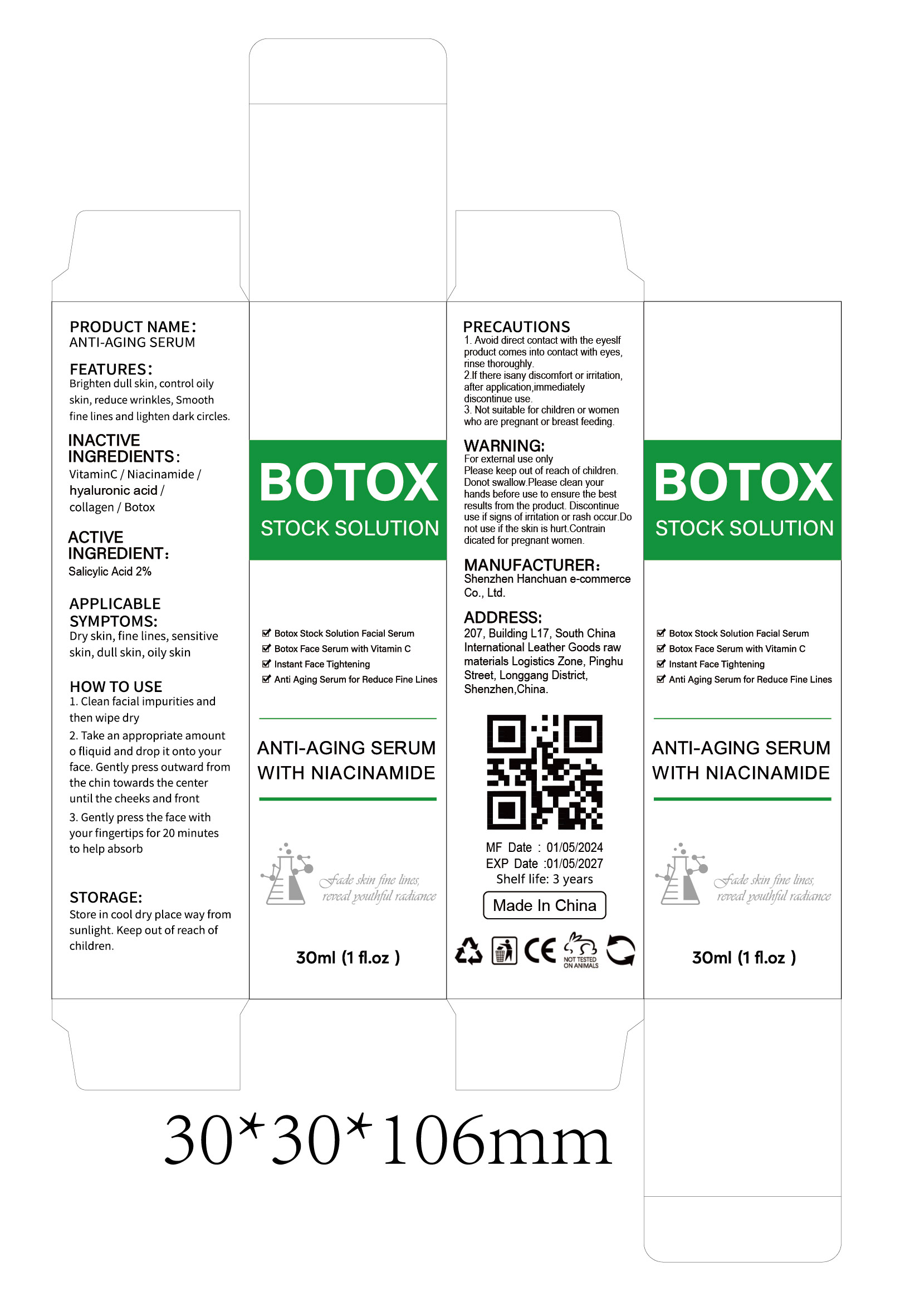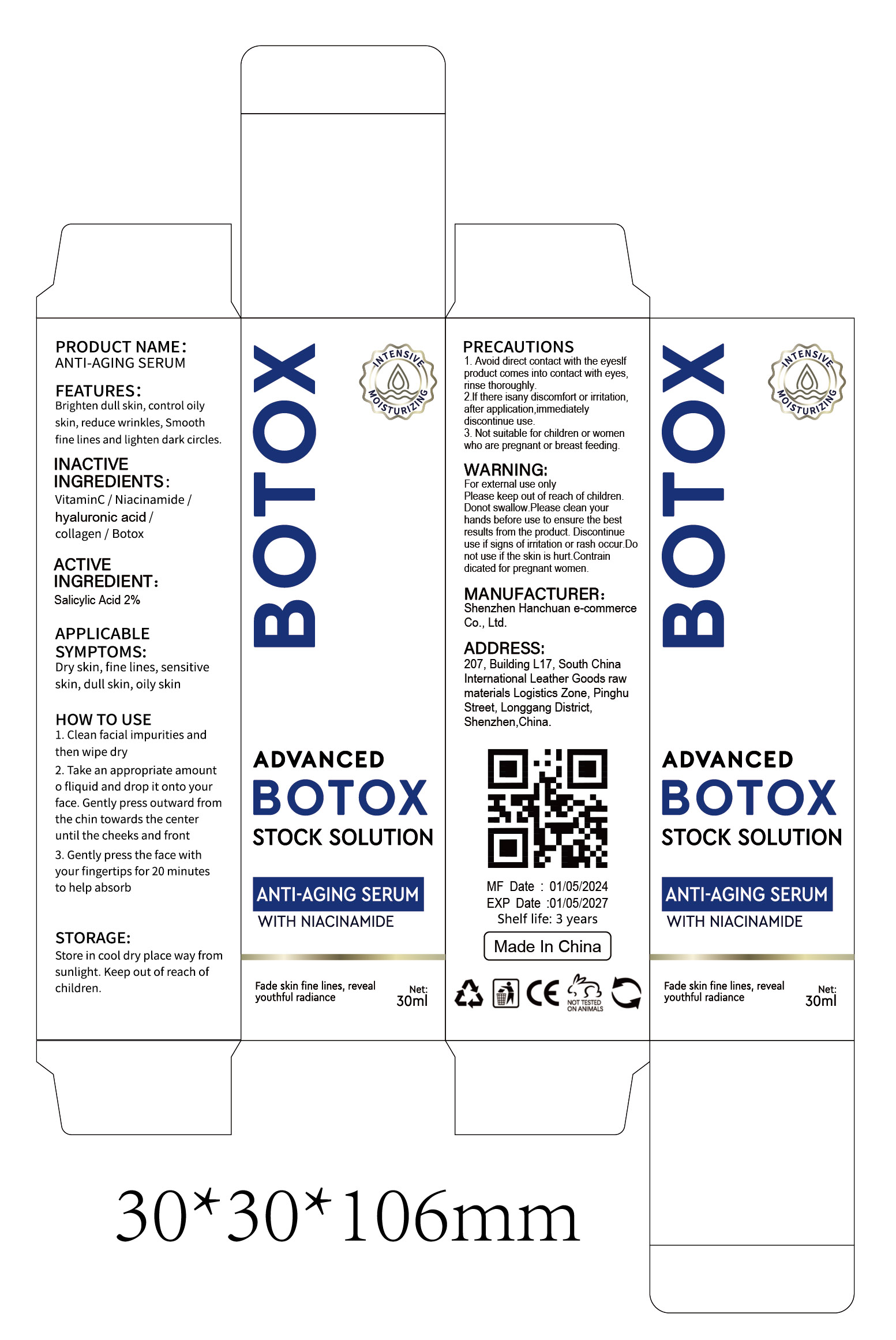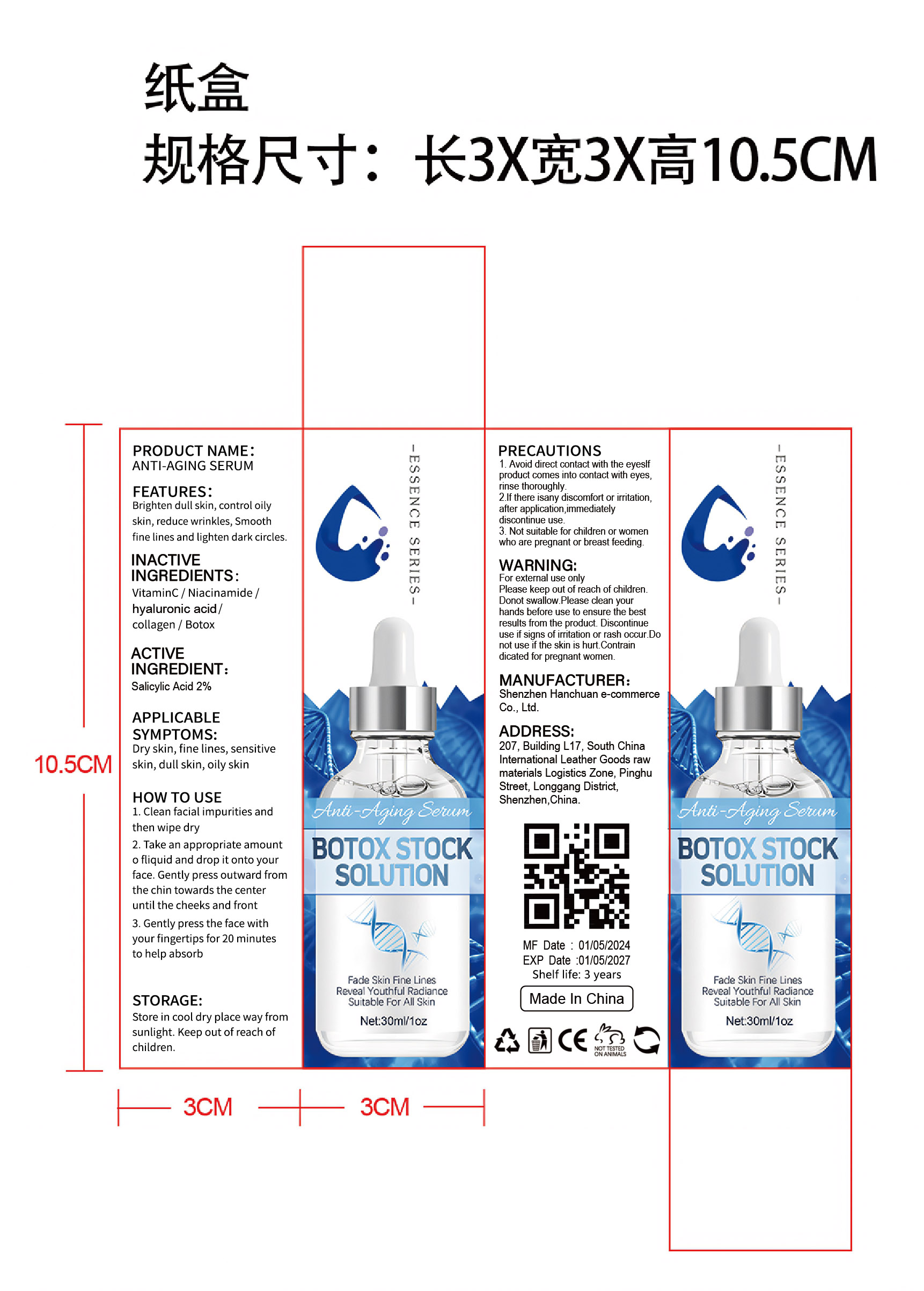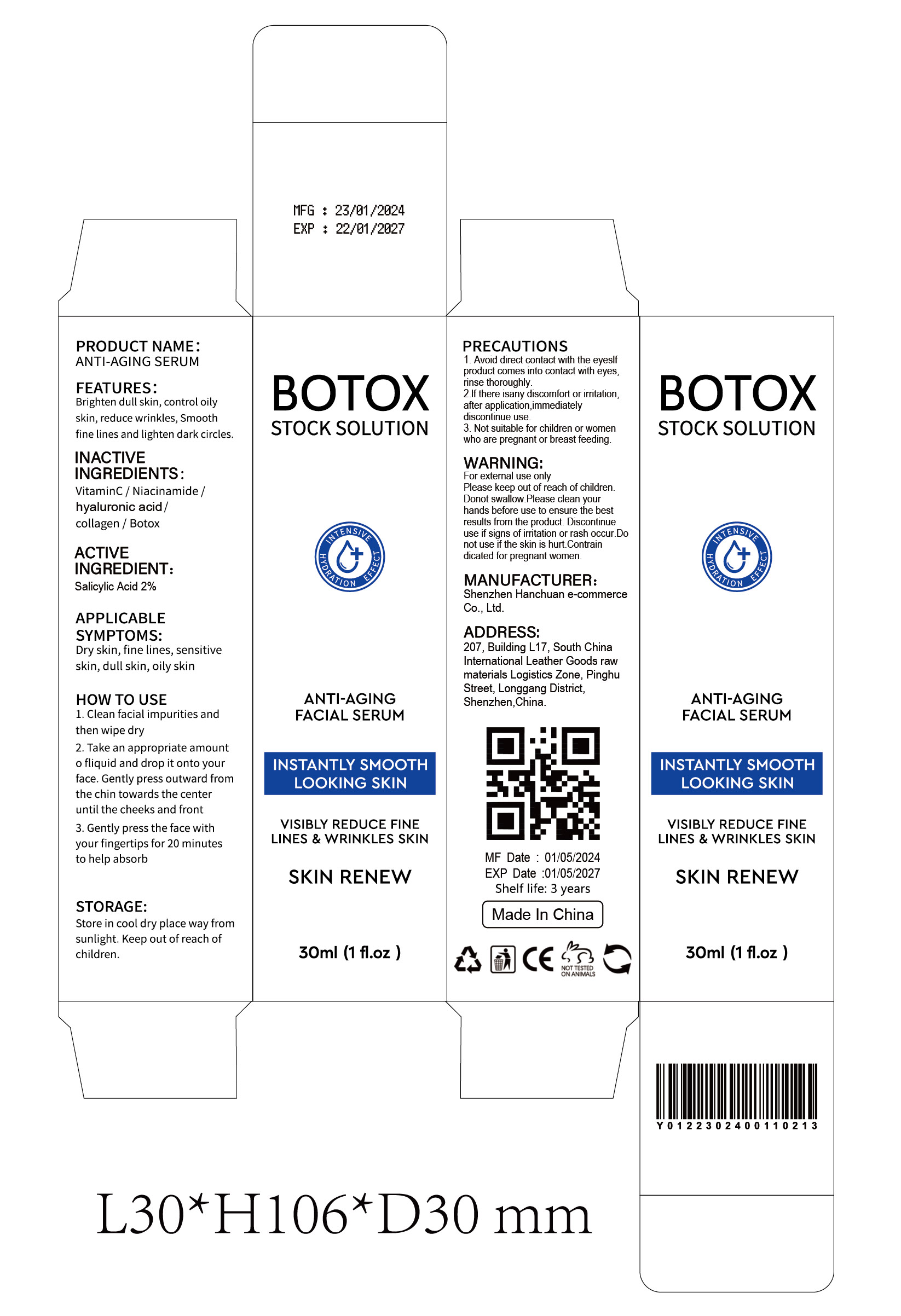 DRUG LABEL: ANTI-AGING
NDC: 84302-002 | Form: LIQUID
Manufacturer: Shenzhen Hanchuan e-commerce Co., Ltd
Category: otc | Type: HUMAN OTC DRUG LABEL
Date: 20240515

ACTIVE INGREDIENTS: SALICYLIC ACID 2 g/100 mL
INACTIVE INGREDIENTS: ASCORBIC ACID; BOTULINUM TOXIN TYPE A; HYALURONIC ACID; NIACINAMIDE; ATELOCOLLAGEN

ANTI-AGING SERUM

ACTIVE INGREDIENT

Salicylic Acid 2%

PURPOSE

Brighten dull skin, control oilyskin, reduce wrinkles, Smoothfine lines and lighten dark circles

Please keep out of reach of children.

INDICATIONS AND USAGE

APPLICABLE
SYMPTOMS:
Dry skin, fine lines, sensitiveskin, dull skin, oily skin

WARNINGS

For external use only
Please keep out of reach of children.Donot swallow.
Please clean yourhands before use to ensure the bestresults from the product. Discontinueuse if signs of irritation or rash occur.
Donot use if the skin is hurt.
Contraindicated for pregnant women.

DOSAGE AND ADMINISTRATION

HOW TO USE
1.Clean facialimpurities andthen wipe dry
2. Take an appropriate amounto fliquid and drop it onto yourface. Gently press outward fromthe chin towards the centeruntil the cheeks and front
3. Gently press the face withyour fingertips for 20 minutesto help absorb

STORAGE AND HANDLING

Store in cool dry place way fromsunlight. Keep out of reach ofchildren.

INACTIVE INGREDIENT

VitaminC
Niacinamide
hyaluronic acid
collagen
Botox